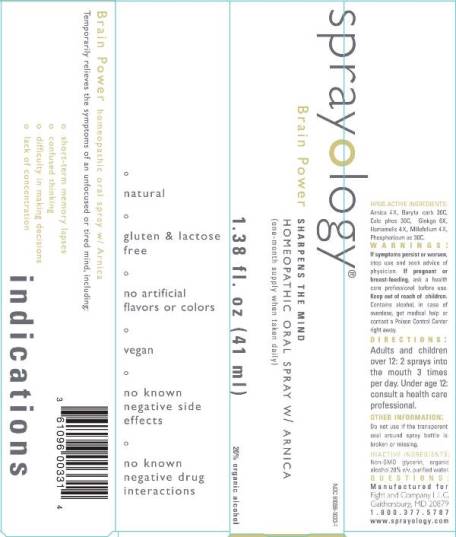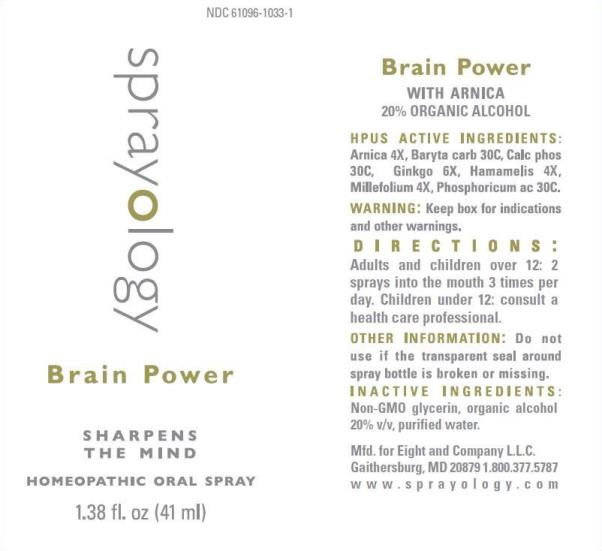 DRUG LABEL: Brain Power
NDC: 61096-1033 | Form: LIQUID
Manufacturer: Eight and Company L.L.C
Category: homeopathic | Type: HUMAN OTC DRUG LABEL
Date: 20251222

ACTIVE INGREDIENTS: ARNICA MONTANA WHOLE 4 [hp_X]/41 mL; BARIUM CARBONATE 30 [hp_C]/41 mL; TRIBASIC CALCIUM PHOSPHATE 30 [hp_C]/41 mL; GINKGO 6 [hp_X]/41 mL; HAMAMELIS VIRGINIANA ROOT BARK/STEM BARK 4 [hp_X]/41 mL; ACHILLEA MILLEFOLIUM WHOLE 4 [hp_X]/41 mL; PHOSPHORIC ACID 30 [hp_C]/41 mL
INACTIVE INGREDIENTS: GLYCERIN; ALCOHOL; WATER

Brain Power

ACTIVE INGREDIENTS:

Arnica 4X, Baryta carb 30C, Calc phos 30C, Ginkgo 6X, Hamamelis 4X, Millefolium 4X, Phosphoricum ac 30C.

PURPOSE:

Temporarily relieves the symptoms of an unfocused or tired mind, including:

- short-term memory lapses
- confused thinking
- difficulty in making decisions
- lack of concentration

WARNINGS:

If symptoms persist or worsen, stop use and seek advice of physician. If pregnant or breast-feeding, ask a health care professional before use. Keep out of reach of children. Contains alcohol, in case of overdose, get medical help or contact a Poison Control Center right away.

Keep out of reach of children. Contains alcohol, in case of overdose, get medical help or contact a Poison Control Center right away.

DIRECTIONS:

- Adults and children over 12: 2 sprays into the mouth 3 times per day.
- Under age 12: consult a health care professional.

OTHER INFORMATION:

Do not use if the transparent seal around spray bottle is broken or missing.

INDICATIONS:

Temporarily relieves the symptoms of an unfocused or tired mind, including:

° short-term memory lapses

° confused thinking

° difficulty in making decisions

° lack of concentration

-natural

-gluten & lactose free

-no artifical flavors or colors

-vegan

° no known negative side effects

° no known negative drug interactions

INACTIVE INGREDIENTS:

Non-GMO glycerin, v/v, organic alcohol 20% v/v and purified water.

QUESTIONS:

Mfd. for Eight and Company L.L.C.

Gaithersburg, MD 20879 1.800.377.5787

www.sprayology.com

PACKAGE LABEL DISPLAY:

NDC 61096-1033-1

sprayology

BRAIN POWER

SHARPENS THE MIND

HOMEOPATHIC ORAL SPRAY

1.38 fl.oz (41 ml)